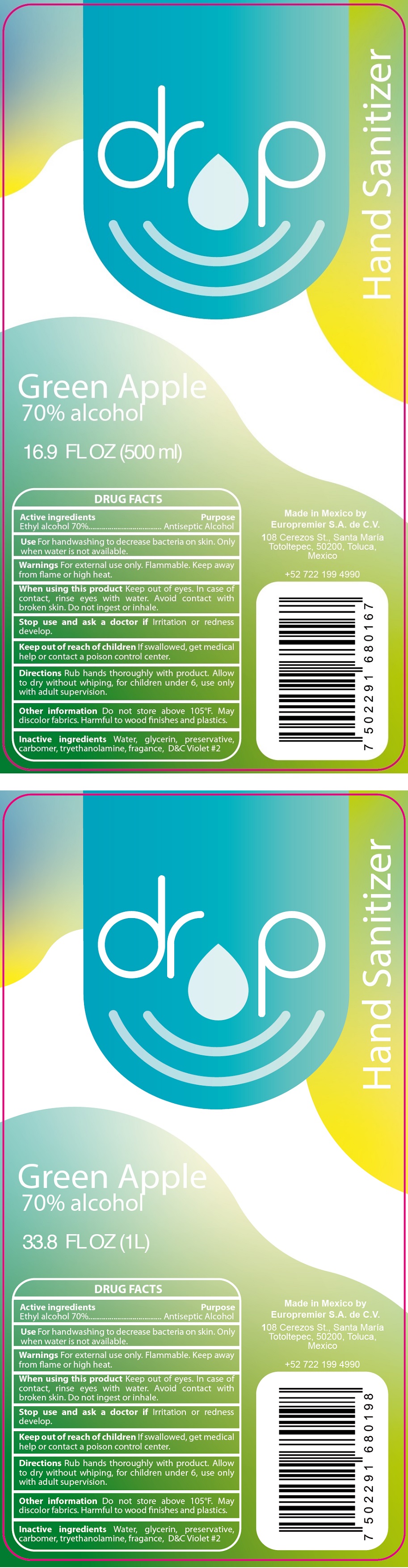 DRUG LABEL: DRP HAND SANITIZER
NDC: 79202-001 | Form: GEL
Manufacturer: Europremier, S.A. de C.V.
Category: otc | Type: HUMAN OTC DRUG LABEL
Date: 20200707

ACTIVE INGREDIENTS: ALCOHOL 70 mL/100 mL
INACTIVE INGREDIENTS: WATER; GLYCERIN; CARBOMER HOMOPOLYMER, UNSPECIFIED TYPE; TROLAMINE; D&C VIOLET NO. 2

drp Hand Sanitizer

Active ingredients

Ethyl alcohol 70%

Purpose

Antiseptic Alcohol

INDICATIONS AND USAGE

Use For handwashing to decrease bacteria on skin. Only when water is not available.

WARNINGS

Warnings For external use only. Flammable. Keep away from flame or high heat.

When using this product Keep out of eyes. In case of contact, rinse eyes with water. Avoid contact with broken skin. Do not ingest or inhale.

Stop use and ask a doctor if Irritation or redness develop.

Keep out of reach of children If swallowed, get medical help or contact a poison control center.

DOSAGE AND ADMINISTRATION

Directions Rub hands thoroughly with product. Allow to dry without whiping, for children under 6, use only with adult supervision.

Other information Do not store above 105°F. May discolor fabrics. Harmful to wood finishes and plastics.

INACTIVE INGREDIENT

Inactive ingredients Water, glycerin, preservative, carbomer, triethanolamine, fragrance, D&C Violet #2

Green Apple

70% alcohol

Made in Mexico by

Europremier S.A. de C.V.

108 Cerezos St., Santa María

Totoltepec, 50200, Toluca,

Mexico

+52 722 199 4990